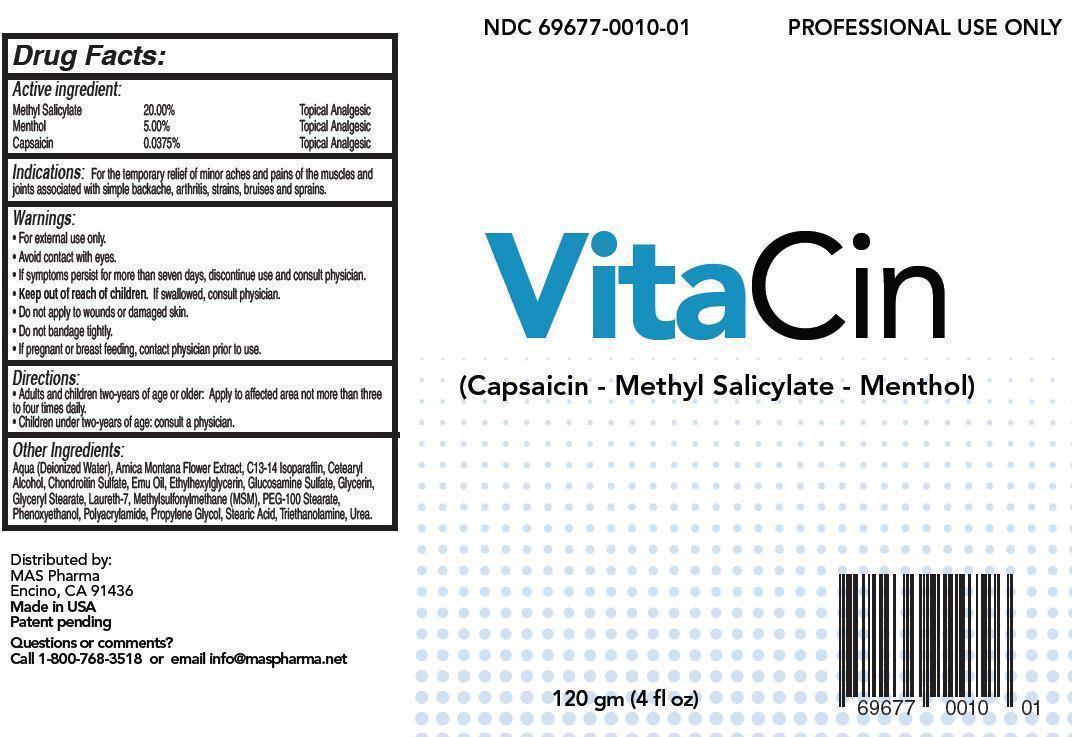 DRUG LABEL: VitaCin
NDC: 69677-010 | Form: CREAM
Manufacturer: MAS Management Group Inc.
Category: otc | Type: HUMAN OTC DRUG LABEL
Date: 20150702

ACTIVE INGREDIENTS: METHYL SALICYLATE 20 g/100 g; MENTHOL 5 g/100 g; CAPSAICIN 0.0375 g/100 g
INACTIVE INGREDIENTS: WATER; ARNICA MONTANA FLOWER; C13-14 ISOPARAFFIN; CETOSTEARYL ALCOHOL; CHONDROITIN SULFATE (BOVINE); EMU OIL; ETHYLHEXYLGLYCERIN; GLUCOSAMINE SULFATE; GLYCERIN; GLYCERYL STEARATE SE; LAURETH-7; DIMETHYL SULFONE; PEG-100 STEARATE; PHENOXYETHANOL; POLYACRYLAMIDE (10000 MW); PROPYLENE GLYCOL; STEARIC ACID; TROLAMINE; UREA

Active Ingredient:

Methyl Salicylate 20.00% Topical Analgesic

Menthol 5.00% Topical Analgesic

Capsaicin 0.0375% Topical Analgesic

PURPOSE

Indications: For the temporary relief of minor aches and pains of the muscles and joints associated with simple backache, arthritis, strains, bruises and sprains.

Keep out of reach of children. If swallowed, consult physician.

INDICATIONS AND USAGE

VitaCin

(Capsaicin - Methyl Salicylate - Menthol)

Directions:

- Adults and children two-years of age or older: Apply to affected area not more than three to four times daily.
- Children under two-years of age: consult a physician.

Warnings:

For external use only.

Avoid contact with eyes.

If symptoms persist for more than seven days, discontinue use and consult physician.

Do not apply to wounds or damaged skin.

Do not bandage tightly.

If pregnant or breast feeding, contact physician prior to use.

INACTIVE INGREDIENT

Other Ingredients:

aqua (deionized water), arnica montana flowe rextract, C13-14 isoparaffin, cetearyl alcohol, chondroitin sulfate, emu oil, ethylhexylglycerin, glucosamine sulfate, glycerin, glyceryl stearate, laureth-7, methylsulfonylmethane (MSM), PEG-100 stearate, phenoxyethanol, polyacrylamide, propylene glycol, stearic acid, triethanolamine, urea.